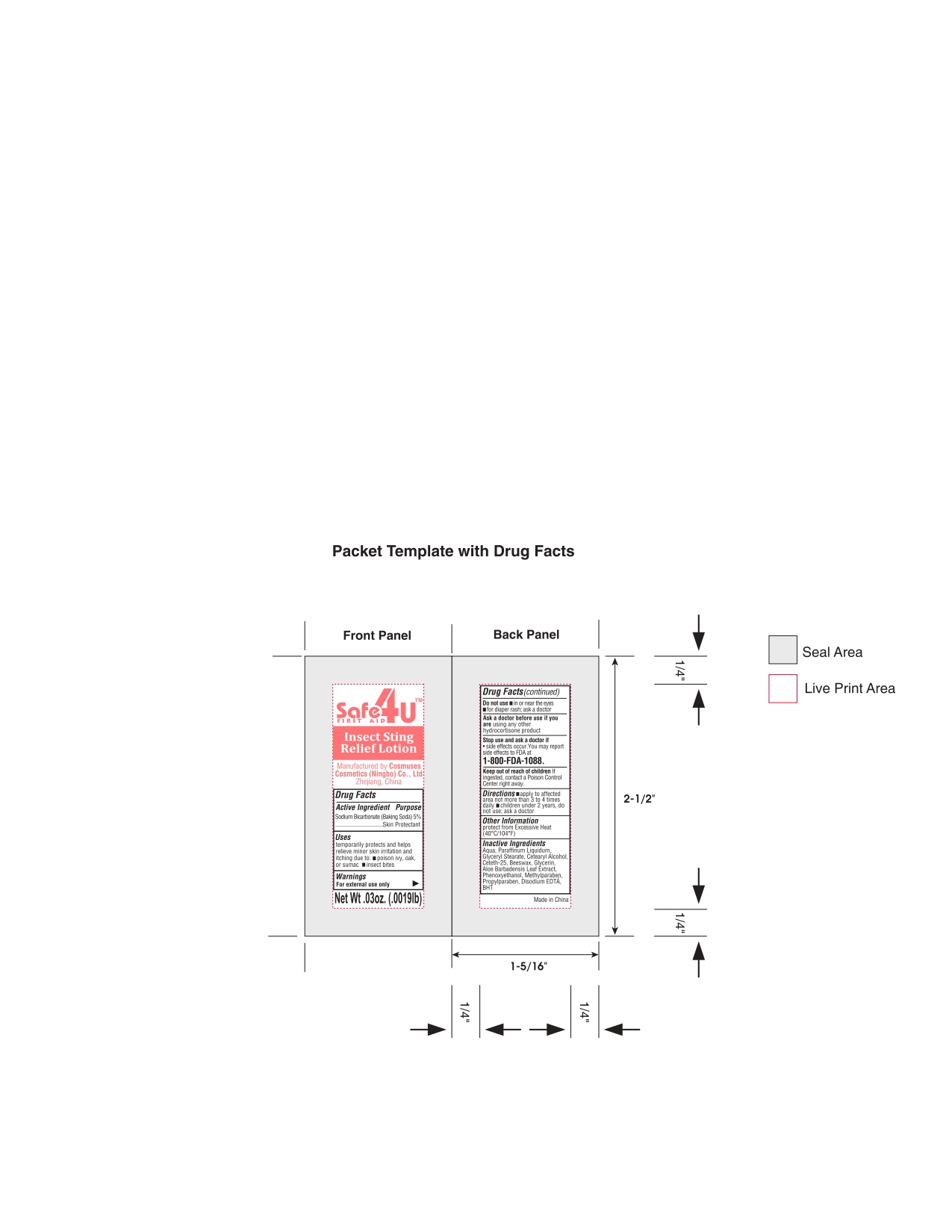 DRUG LABEL: Insect sting relief latex
NDC: 82953-020 | Form: LOTION
Manufacturer: Cosmuses Cosmetics (Ningbo) Co., Ltd.
Category: otc | Type: HUMAN OTC DRUG LABEL
Date: 20240819

ACTIVE INGREDIENTS: SODIUM BICARBONATE 5 g/100 g
INACTIVE INGREDIENTS: YELLOW WAX; GLYCERYL MONOSTEARATE; PROPYLPARABEN; CETOSTEARYL ALCOHOL; EDETATE DISODIUM; GLYCERIN; WATER; ALOE VERA LEAF; PHENOXYETHANOL; METHYLPARABEN; MINERAL OIL; CETETH-25; BUTYLATED HYDROXYTOLUENE

insect sting relief lotion

Drug Fact

Active Ingredient

Sodium bicarbonate (Baking Soda) 5%

Purpose

Skin Protectant

Uses

temporary protects and helps relieve minor skin irritation and itching due to:

- poison ivy, oak, or sumac
- insect bites

Warnings

- For external use only.

Do not use

- in or near the eyes
- for diaper rash; ask a doctor

Ask a doctor before use if you are

using any other hydrocortisone product

Stop use and ask a doctor if

- side effects occur. You may report side effects to FDA at
- 1-800-FDA-1088.

Keep out of reach of children if ingested, contact a poison control center right away.

Directions

- apply to affected area not more than 3 to 4 times daily
- children under 2 years, do not use; ask a doctor

Other information

protect from Excessive Heat: (40℃/104℉)

Inactive Ingredients

Aqua, Paraffinum Liquidum, Glyceryl Stearate, Cetearyl Alcohol, Ceteth-25, Beeswax, Glycerin, Aloe Barbadensis Leaf Extract, Phenoxyethanol, Methylparaben, Propylparaben, Disodium EDTA, BHT.